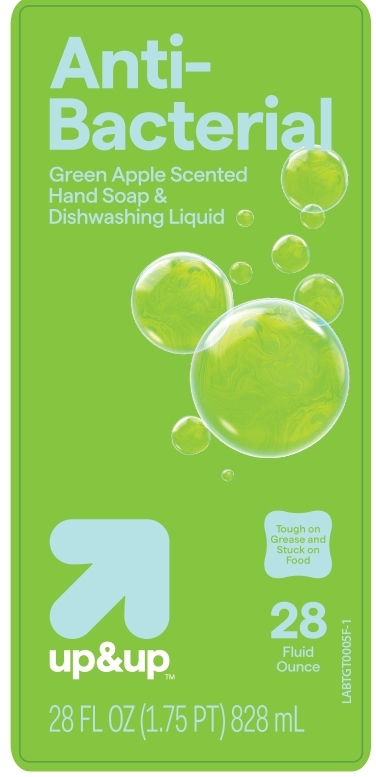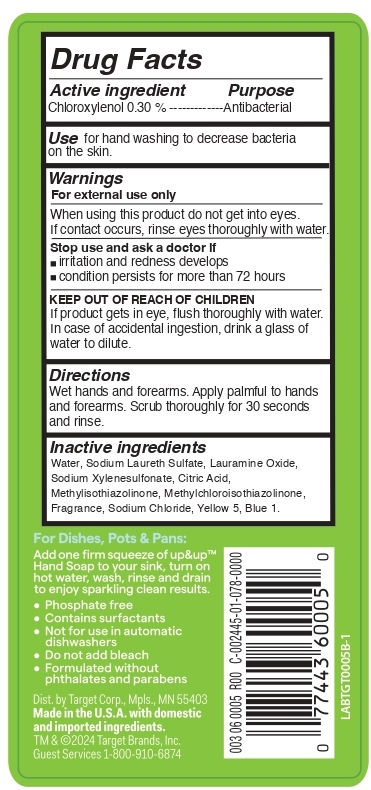 DRUG LABEL: Chloroxylenol 0.30 %
NDC: 42669-028 | Form: LIQUID
Manufacturer: Davion, Inc
Category: otc | Type: HUMAN OTC DRUG LABEL
Date: 20250215

ACTIVE INGREDIENTS: CHLOROXYLENOL 3 mg/1 mL
INACTIVE INGREDIENTS: WATER; SODIUM LAURETH-3 SULFATE; LAURAMINE OXIDE; SODIUM XYLENESULFONATE; CITRIC ACID; METHYLISOTHIAZOLINONE; Methylchloroisothiazolinone; Sodium Chloride; FD&C YELLOW NO. 5; FD&C BLUE NO. 1

Antibacterial Green Apple Scented Hand Soap and Dishwashing Liquid

Active ingredient

Chloroxylenol 0.30 %

Purpose

Antibacterial

Use

for hand washing to decrease bacteria on the skin.

Warnings

For external use only

When using this product do not get into eyes. If contact occurs, rinse eyes thoroughly with water.

Stop use and ask a doctor if

- irritation and redness develops
- condition persists for more than 72 hours

KEEP OUT OF REACH OF CHILDREN. If product gets in eye, flush thoroughly with water. In case of accidental ingestion, drink a glass of water to dilute.

Directions

Wet hands and forearms. Apply palmful to hands and forearms. Scrub thoroughly for 30 seconds and rinse.

Inactive ingredients

Water, Sodium Laureth Sulfate, Lauramine Oxide, Sodium Xylenesulfonate, Citric Acid, Methylisothiazolinone, Methylchloroisothiazolinone,
Fragrance, Sodium Chloride, Yellow 5, Blue 1.